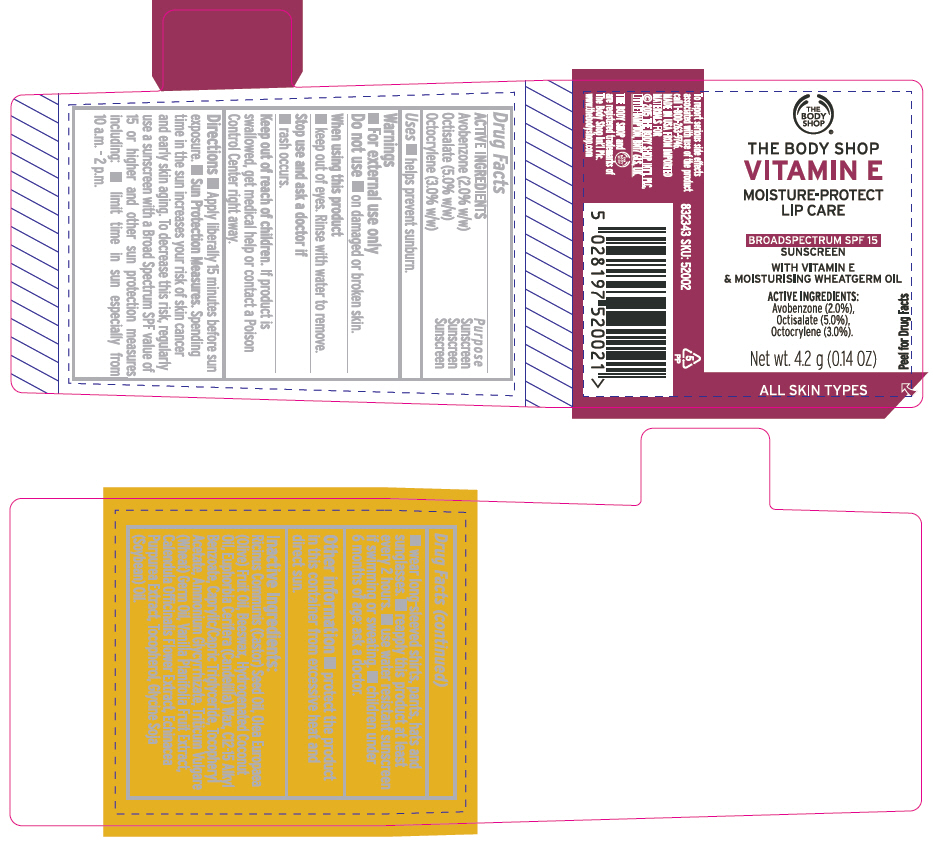 DRUG LABEL: VITAMIN E MOISTURE-PROTECT LIP CARE SPF 15
NDC: 57691-002 | Form: STICK
Manufacturer: The Body Shop, Wake Forest
Category: otc | Type: HUMAN OTC DRUG LABEL
Date: 20160318

ACTIVE INGREDIENTS: Octisalate 0.05 g/1 g; Avobenzone 0.02 g/1 g; Octocrylene 0.03 g/1 g
INACTIVE INGREDIENTS: CASTOR OIL; OLIVE OIL; YELLOW WAX; Hydrogenated Coconut Oil; CANDELILLA WAX; ALKYL (C12-15) BENZOATE; MEDIUM-CHAIN TRIGLYCERIDES; .ALPHA.-TOCOPHEROL ACETATE; Ammonium Glycyrrhizate; WHEAT GERM OIL; Vanilla; Calendula Officinalis Flower; Echinacea Purpurea; Tocopherol; SOYBEAN OIL

VITAMIN E MOISTURE-PROTECT LIP CARE SPF 15

Drug Facts

ACTIVE INGREDIENT

ACTIVE INGREDIENTS | Purpose
Avobenzone (2.0% w/w) | Sunscreen
Octisalate (5.0% w/w) | Sunscreen
Octocrylene (3.0% w/w) | Sunscreen

Uses

- helps prevent sunburn.

Warnings

- For external use only

Do not use

- on damaged or broken skin.

When using this product

- keep out of eyes. Rinse with water to remove.

Stop use and ask a doctor if

- rash occurs.

Keep out of reach of children. If product is swallowed, get medical help or contact a Poison Control Center right away.

Directions

- Apply liberally 15 minutes before sun exposure.
- Sun Protection Measures. Spending time in the sun increases your risk of skin cancer and early skin aging. To decrease this risk, regularly use a sunscreen with a Broad Spectrum SPF value of 15 or higher and other sun protection measures including:
- limit time in sun especially from 10 a.m. – 2 p.m.
- wear long-sleeved shirts, pants, hats and sunglasses.
- reapply this product at least every 2 hours.
- use water resistant sunscreen if swimming or sweating.
- children under 6 months of age: ask a doctor.

Other information

- protect the product in this container from excessive heat and direct sun.

Inactive Ingredients

Ricinus Communis (Castor) Seed Oil, Olea Europaea (Olive) Fruit Oil, Beeswax, Hydrogenated Coconut Oil, Euphorbia Cerifera (Candelilla) Wax, C12-15 Alkyl Benzoate, Caprylic/Capric Triglyceride, Tocopheryl Acetate, Ammonium Glycyrrhizate, Triticum Vulgare (Wheat) Germ Oil, Vanilla Planifolia Fruit Extract, Calendula Officinalis Flower Extract, Echinacea Purpurea Extract, Tocopherol, Glycine Soja (Soybean) Oil.

PRINCIPAL DISPLAY PANEL - 4.2 g Container

THE
BODY
SHOP®

THE BODY SHOP
VITAMIN E
MOISTURE-PROTECT
LIP CARE

BROADSPECTRUM SPF 15
SUNSCREEN

WITH VITAMIN E
& MOISTURISING WHEATGERM OIL

ACTIVE INGREDIENTS:
Avobenzone (2.0%),
Octisalate (5.0%),
Octocrylene (3.0%).

Net wt. 4.2 g (0.14 OZ)

ALL SKIN TYPES

Peel for Drug Facts